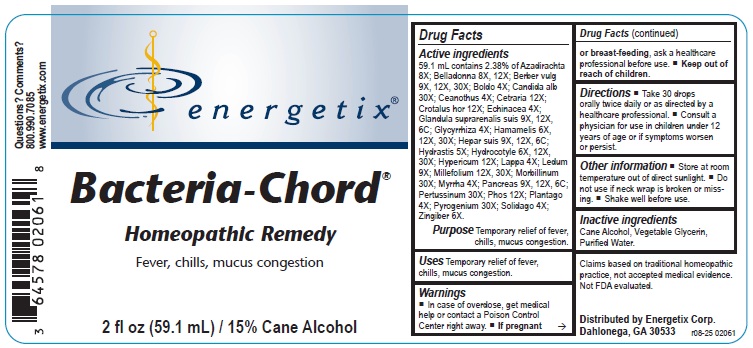 DRUG LABEL: Bacteria-Chord
NDC: 64578-0158 | Form: LIQUID
Manufacturer: Energetix Corporation
Category: homeopathic | Type: HUMAN OTC DRUG LABEL
Date: 20251217

ACTIVE INGREDIENTS: AZADIRACHTA INDICA BARK 8 [hp_X]/59.1 mL; ATROPA BELLADONNA 8 [hp_X]/59.1 mL; BERBERIS VULGARIS ROOT BARK 9 [hp_X]/59.1 mL; PEUMUS BOLDUS LEAF 4 [hp_X]/59.1 mL; CANDIDA ALBICANS 30 [hp_X]/59.1 mL; CEANOTHUS AMERICANUS LEAF 4 [hp_X]/59.1 mL; CETRARIA ISLANDICA WHOLE 12 [hp_X]/59.1 mL; CROTALUS HORRIDUS HORRIDUS VENOM 12 [hp_X]/59.1 mL; ECHINACEA, UNSPECIFIED 4 [hp_X]/59.1 mL; SUS SCROFA ADRENAL GLAND 9 [hp_X]/59.1 mL; GLYCYRRHIZA GLABRA 4 [hp_X]/59.1 mL; HAMAMELIS VIRGINIANA ROOT BARK/STEM BARK 6 [hp_X]/59.1 mL; PORK LIVER 9 [hp_X]/59.1 mL; GOLDENSEAL 5 [hp_X]/59.1 mL; CENTELLA ASIATICA 6 [hp_X]/59.1 mL; HYPERICUM PERFORATUM WHOLE 12 [hp_X]/59.1 mL; ARCTIUM LAPPA ROOT 4 [hp_X]/59.1 mL; RHODODENDRON TOMENTOSUM LEAFY TWIG 9 [hp_X]/59.1 mL; ACHILLEA MILLEFOLIUM WHOLE 12 [hp_X]/59.1 mL; MEASLES VIRUS 30 [hp_X]/59.1 mL; MYRRH 4 [hp_X]/59.1 mL; SUS SCROFA PANCREAS 9 [hp_X]/59.1 mL; HUMAN SPUTUM, BORDETELLA PERTUSSIS INFECTED 30 [hp_X]/59.1 mL; PHOSPHORUS 12 [hp_X]/59.1 mL; PLANTAGO MAJOR 4 [hp_X]/59.1 mL; RANCID BEEF 30 [hp_X]/59.1 mL; SOLIDAGO VIRGAUREA FLOWERING TOP 4 [hp_X]/59.1 mL; GINGER 6 [hp_X]/59.1 mL
INACTIVE INGREDIENTS: ALCOHOL; GLYCERIN; WATER

Bacteria-Chord

Active ingredients

59.1 mL contains 2.38% of Azadirachta 8X; Belladonna 8X, 12X; Berber vulg 9X, 12X, 30X; Boldo 4X; Candida alb 30X; Ceanothus 4X; Cetraria 12X; Crotalus hor 12X; Echinacea 4X; Glandula suprarenalis suis 9X, 12X, 6C; Glycyrrhiza 4X; Hamamelis 6X, 12X, 30X; Hepar suis 9X, 12X, 6C;
Hydrastis 5X; Hydrocotyle 6X, 12X, 30X; Hypericum 12X; Lappa 4X; Ledum 9X; Millefolium 12X, 30X; Morbillinum 30X; Myrrha 4X; Pancreas 9X, 12X, 6C; Pertussinum 30X; Phos 12X; Plantago 4X; Pyrogenium 30X; Solidago 4X; Zingiber 6X.

Claims based on traditional homeopathic practice, not accepted medical evidence. Not FDA evaluated.

Uses

Temporary relief of fever, chills, mucus congestion.

Warnings

- In case of overdose, get medica help or contact a Poison Control Center right away.
- If pregnant or breast-feeding, ask a healthcare professional before use.

- Keep out of reach of children.

Directions

- Take 30 drops orally twice daily or as directed by a healthcare professional.
- Consult a physician for use in children under 12 years of age or if symptoms worsen or persist.

Other information

- Store at room temperature out of direct sunlight.
- Do not use if neck wrap is broken or missing.
- Shake well before use.

Inactive ingredients

Cane Alcohol, Vegetable Glycerin, Purifed Water

QUESTIONS

Distributed by Energetix Corp.

Dahlonega, GA 30533

Questions? Comments?

800.990.7085

www.energetix.com

PACKAGE LABEL

energetix

Bacteria-Chord

Homeoapathic Remedy

Fever, chills, mucus congestion

2 fl oz (59.1 mL) / 15% Cane Alcohol

Purpose

Temporary relief of fever, chills, mucus congestion